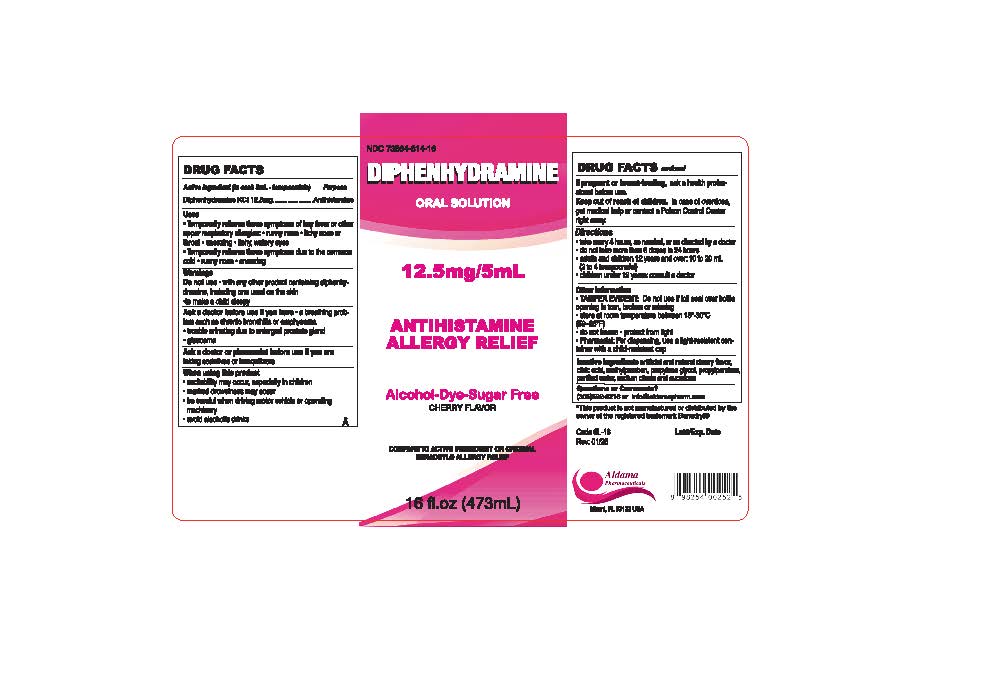 DRUG LABEL: Diphenhydramine Oral Solution
NDC: 73564-814 | Form: SOLUTION
Manufacturer: Aldama Pharmaceuticals, Inc
Category: otc | Type: HUMAN OTC DRUG LABEL
Date: 20260121

ACTIVE INGREDIENTS: DIPHENHYDRAMINE HYDROCHLORIDE 12.5 mg/5 mL
INACTIVE INGREDIENTS: WATER; SUCRALOSE; ANHYDROUS CITRIC ACID; PROPYLENE GLYCOL; METHYLPARABEN; PROPYLPARABEN; SODIUM CITRATE

Diphenhydramine Oral Solution

Active ingredient (in each 5 mL-teaspoonful)

Diphenhydramine KCI 12.5mg

Purpose

Antihistamine

Uses

- Temporarily relieves these symptoms of hay fever or other upper respiratory allergies:
  - runny nose
  - itchy nose or throat
  - sneezing
  - itchy, watery eyes

Temporarily relieves these symptoms due to the common cold

- runny nose
- sneezing

Warnings

Do not use

with any other drug containing diphenhydramine, including one used on the skin.
to make a child sleepy

Do not use

- with any other drug containing diphenhydramine, including one used on the skin.
- to make a child sleepy

Ask a doctor before use if you have

- a breathing problem such as chronic bronchitis or emphysema
- trouble urinating due to enlarged prostate gland
- glaucoma

Ask a doctor or pharmacist before use if you are

taking sedatives or tranquilizers

When using this product

- excitability may occur, especially in children
- marked drowsiness may occur
- be careful when driving motor vehicle or operating machinery
- avoid alcoholic drinks

If pregnant or breast-feeding

ask a health professional before use

Keep out of reach of children.

In case of overdose, get medical help or contact a Poison Control Center right away.

Directions

- Take every 4 hours, as needed, or as directed by a doctor
- Do not take more than 6 doses in 24 hours
- adults and children 12 years and over: 10 to 20 ml 2 to 4 teaspoonsful
- Children under 12 years: consult a doctor

Other information

- TAMPER EVIDENT: Do not use if foil seal over bottle opening is torn, broken or missing
- store at room temperature between 15-30°C (59-86°F)
- do not freeze
- protect from light
- Pharmacist: For dispensing, use a light-resistent container with a child-resistant cap

Inactive Ingredient

artificial and natural cherry flavor, citric acid, methylparaben, propylene glycol, propylparaben, purified water, sodium citrate, sucralose

Question or Comments?

305-592-9216 or info@aldamapharm.com